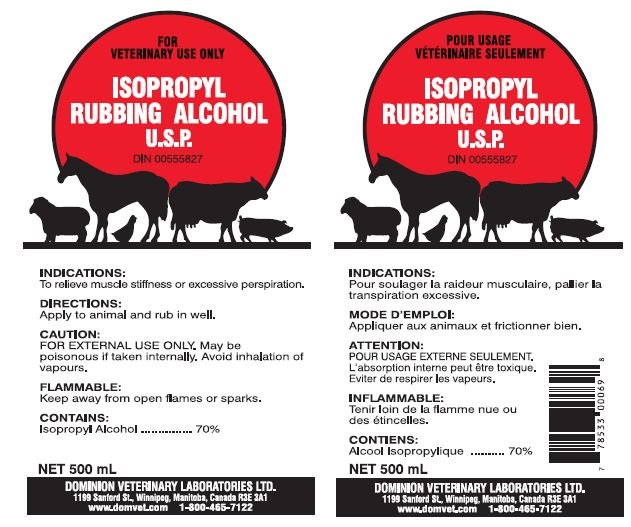 DRUG LABEL: ISOPROPYL RUBBING ALCOHOL
NDC: 64120-103 | Form: SOLUTION
Manufacturer: DOMINION VETERINARY LABORATORIES LTD.
Category: animal | Type: OTC ANIMAL DRUG LABEL
Date: 20211108

ACTIVE INGREDIENTS: ISOPROPYL ALCOHOL 70 mL/100 mL
INACTIVE INGREDIENTS: WATER

DOMINION VETERINARY LABORATORIES - ISOPROPYL RUBBING ALCOHOL USP

INDICATIONS:

TO RELIEVE MUSCLE STIFFNESS OR EXCESSIVE PERSPIRATION.